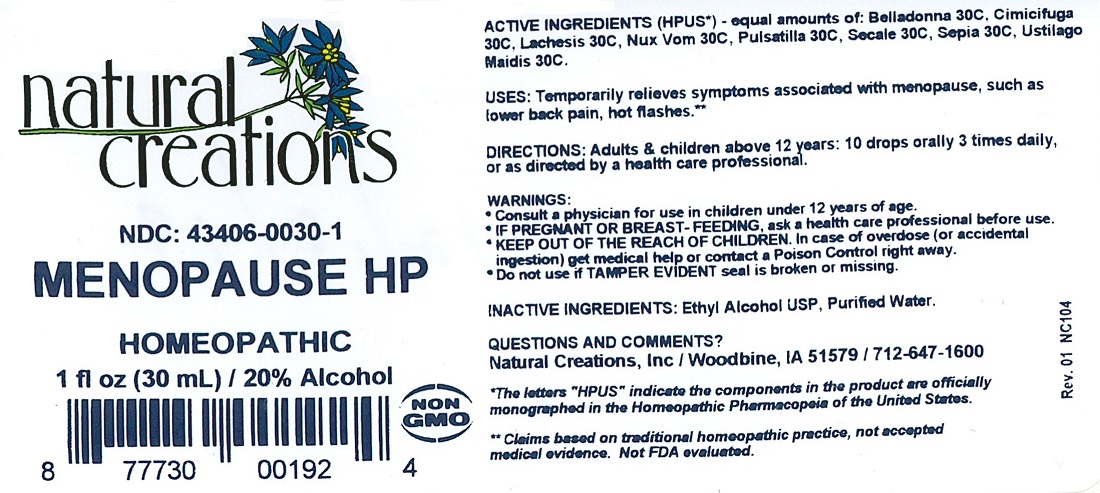 DRUG LABEL: MENOPAUSE HP
NDC: 43406-0030 | Form: LIQUID
Manufacturer: Natural Creations, Inc.
Category: homeopathic | Type: HUMAN OTC DRUG LABEL
Date: 20251216

ACTIVE INGREDIENTS: ATROPA BELLADONNA 30 [hp_C]/1 mL; BLACK COHOSH 30 [hp_C]/1 mL; LACHESIS MUTA VENOM 30 [hp_C]/1 mL; STRYCHNOS NUX-VOMICA SEED 30 [hp_C]/1 mL; PULSATILLA VULGARIS 30 [hp_C]/1 mL; CLAVICEPS PURPUREA SCLEROTIUM 30 [hp_C]/1 mL; SEPIA OFFICINALIS JUICE 30 [hp_C]/1 mL; USTILAGO MAYDIS 30 [hp_C]/1 mL
INACTIVE INGREDIENTS: WATER; ALCOHOL

MENOPAUSE HP

ACTIVE INGREDIENT

ACTIVE INGREDIENTS (HPUS*) - equal amounts of: Belladonna 30C, Cimicifuga Racemosa 30C, Lachesis Mutus 30C, Nux Vomica 30C, Pulsatilla 30C, Secale Cornutum 30C, Sepia 30C, Ustilago Maidis 30X

INDICATIONS AND USAGE

USES: Temporarily relieves symptoms associated with menopause, such as lower back pain, hot flashes.**

WARNING:

*Consult a physician for us in children under 12 years of age.

* IF PREGNANT OR BREAST-FEEDING, ask a health care professional before use.

* KEEP OUT OF THE REACH OF CHILDREN. In case of overdose (or accidental ingestion) get medical help or contact a Poison Control Center right away.

* Do not use if TAMPER EVIDENT seal is broken or missing.

DOSAGE AND ADMINISTRATION

DIRECTIONS: Adults and children above 12 years: 10 drops orally 3 times daily, or as directed by a health care professional.

REFERENCES

INACTIVE INGREDIENTS: Ethyl Alcohol USP, Purified Water.

INACTIVE INGREDIENTS: Ethyl Alcohol USP, Purified Water.

QUESTIONS AND COMMENTS?

MFG FOR: Natural Creations, Inc. / Woodbine, IA 51579 / 712-647-1600

PURPOSE

USES: Temporarily relieves symptoms associated with menopause, such as lower back pain, hot flashes.**

KEEP OUT OF REACH OF CHILDREN

KEEP OUT OF THE REACH OF CHILDREN. In case of overdose (or accidental ingestion) get medical help or contact a Poison Control Center.

PACKAGE LABEL

NDC: 43406-0030-1

MENOPAUSE HP

HOMEOPATHIC

1 fl oz (30 mL) / 20% Alcohol